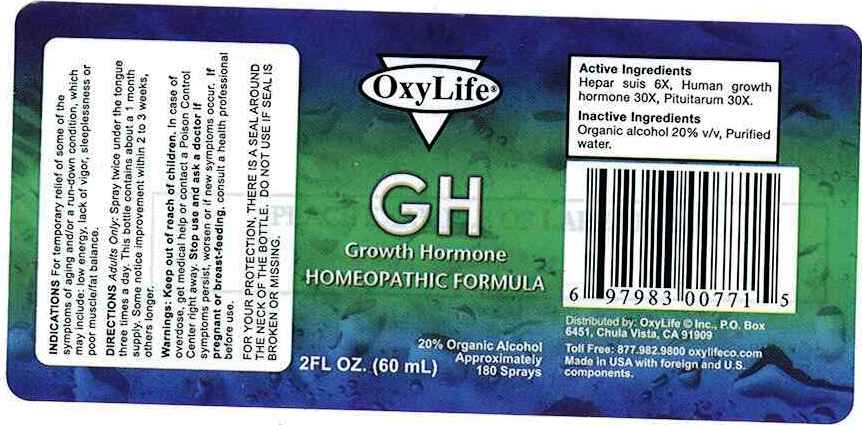 DRUG LABEL: GH
NDC: 50845-0133 | Form: SPRAY
Manufacturer: Liddell Laboratories, Inc.
Category: homeopathic | Type: HUMAN OTC DRUG LABEL
Date: 20110620

ACTIVE INGREDIENTS: PORK LIVER 6 [hp_X]/1 mL; SOMATROPIN 30 [hp_X]/1 mL; SUS SCROFA PITUITARY GLAND 30 [hp_X]/1 mL
INACTIVE INGREDIENTS: WATER; ALCOHOL

GH

ACTIVE INGREDIENT

ACTIVE INGREDIENTS: Hepar suis 6X, Human Growth Hormone 30X, Pituitary suis 30X.

PURPOSE

INDICATIONS: For temporary relief of some of the symptoms of aging and/or a run-down condition, which may include: low energy, lack of vigor, sleeplessness or poor muscle/fat balance.

WARNINGS

WARNINGS: Keep out of reach of children. In case of overdose, get medical help or contact a Poison Control Center right away.

Stop use and ask a doctor if symptoms persist, worsen or if new symptoms occur

If pregnant or breast-feeding, consult a health professional before use.

FOR YOUR PROTECTION, THERE IS A SEAL AROUND THE NECK OF THE BOTTLE. DO NOT USE IF SEAL IS BROKEN OR MISSING.

DOSAGE AND ADMINISTRATION

DIRECTIONS: Adults Only: Spray twice under the tongue three times a day. This bottle contains about a 1 month supply. Some notice improvement within 2 to 3 weeks, others longer.

INACTIVE INGREDIENT

INACTIVE INGREDIENTS: Organic alcohol 20% v/v, Purified water.

KEEP OUT OF REACH OF CHILDREN. In case of overdose, get medical help or contact a Poison Control Center right away.

INDICATIONS AND USAGE

INDICATIONS: For temporary relief of some of the symptoms of aging and/or a run-down condition, which may include: low energy, lack of vigor, sleeplessness or poor muscle/fat balance.

QUESTIONS

Distributed by: OxyLife, Inc.

P.O. Box 6451

Chula Vista, CA 91909

Toll free: 877-982-9800

oxylife.com

Made in USA with foreign and U.S. components.

PACKAGE LABEL

OxyLife

GH

Growth Hormone

HOMEOPATHIC FORMULA

2 FL OZ. (60mL)

Approximately 180 sprays